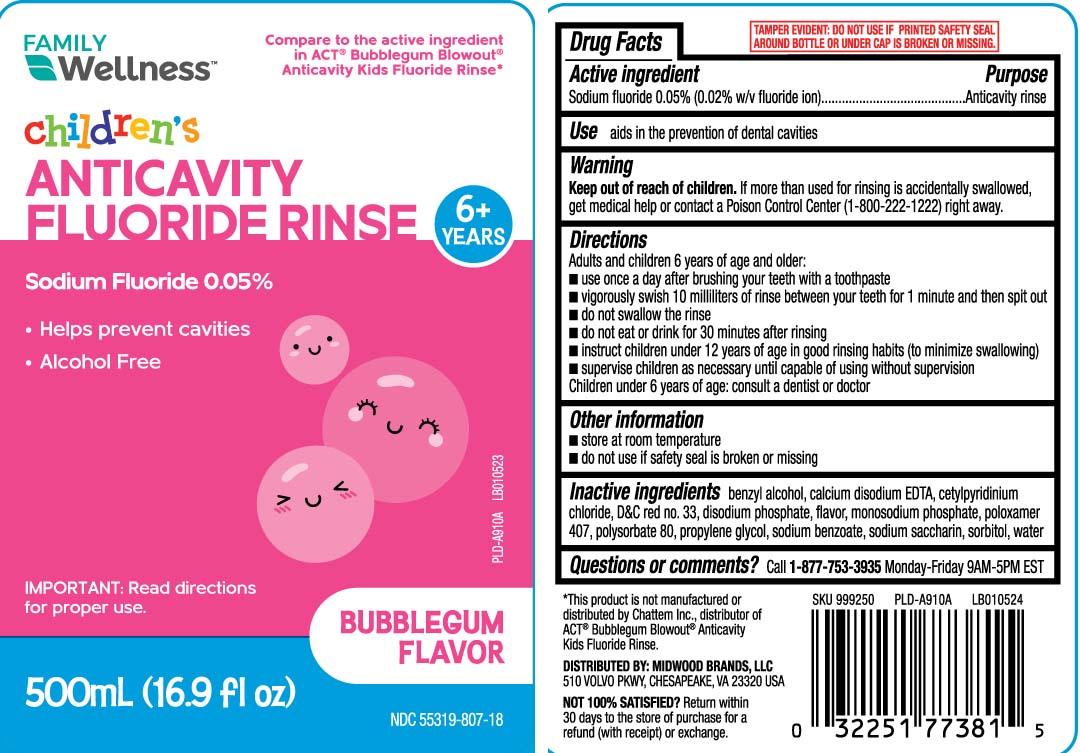 DRUG LABEL: Anticavity Fluoride
NDC: 55319-807 | Form: MOUTHWASH
Manufacturer: Family Dollar (FAMILY WELLNESS)
Category: otc | Type: HUMAN OTC DRUG LABEL
Date: 20251009

ACTIVE INGREDIENTS: SODIUM FLUORIDE 0.05 mg/1 mL
INACTIVE INGREDIENTS: WATER; SORBITOL; PROPYLENE GLYCOL; POLOXAMER 407; BENZYL ALCOHOL; DISODIUM PHOSPHATE; SODIUM BENZOATE; SODIUM SACCHARIN; POLYSORBATE 80; CETYLPYRIDINIUM CHLORIDE; CALCIUM DISODIUM EDTA; D&C RED NO. 33; SODIUM PHOSPHATE, MONOBASIC, UNSPECIFIED FORM

Childrens Anticavity Fluoride Rinse

Active ingredient

Sodium fluoride 0.05% (0.02% w/v fluoride ion)

Purpose

Anticavity rinse

Uses

aids in the prevention of dental cavities

Warnings

Keep out of reach of children.

If more than used for rinsing is accidentally swallowed, get medical help or contact a Poison Control Center (1-800-222-1222) right away.

Directions

Adults and children 6 years of age and older:
■ use once a day after brushing your teeth with a toothpaste
■ vigorously swish 10 milliliters of rinse between your teeth for 1 minute and then spit out
■ do not swallow the rinse
■ do not eat or drink for 30 minutes after rinsing
■ instruct children under 12 years of age in good rinsing habits (to minimize swallowing)
■ supervise children as necessary until capable of using without supervision
Children under 6 years of age: consult a dentist or doctor

Other information

■ store at room temperature
■ do not use if safety seal is broken or missing

Inactive ingredients

water, sorbitol, propylene glycol, flavor, poloxamer 407, monosodium phosphate, benzyl alcohol, disodium phosphate, sodium benzoate, sodium saccharin, polysorbate 80, cetylpyridinium chloride, calcium disodium EDTA, D&C red no. 33

Questions or comments?

Call 1-877-753-3935 Monday-Friday 9AM-5PM EST

Principal display panel

Compare to the active ingredient in ACT® Bubblegum Blowout® Anticavity Kids Fluoride Rinse*

Children's

ANTICAVITY

FLUORIDE RINSE

6+ YEARS

Sodium Fluoride 0.05%

- Help prevent cavities
- Alcohol Free

IMPORTANT: Read directions for proper use.

BUBBLEGUM FLAVOR

TAMPER EVIDENT: DO NOT USE IF PRINTER SAFETY SEAL AROUND BOTTLE OR UNDER CAP IS BROKEN OR MISSING.

*This product is not manufactured or distributed by Chattem Inc., distributor of ACT® Bubblegum Blowout® Anticavity Kids Fluoride Rinse

DISTRIBUTED BY: MIDWOOD BRANDS, LLC

510 VOLVO PKWY, CHESAPEAKE, VA 23320

Package label

FAMILY WELLNESS Children's Anticavity Fluoride Rinse Bubble Gum